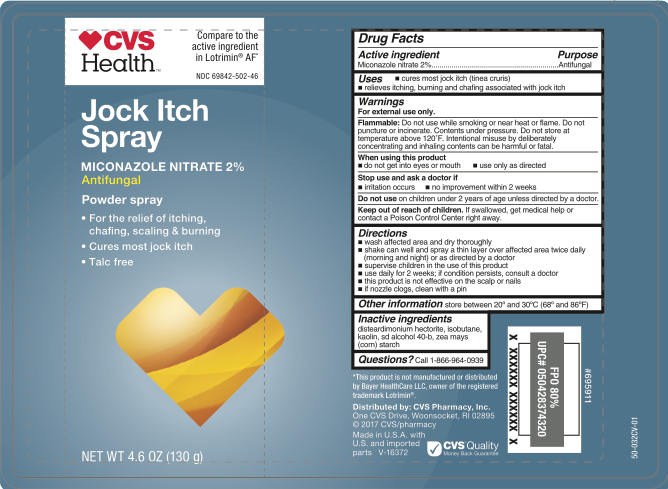 DRUG LABEL: Miconazole Nitrate
NDC: 69842-502 | Form: AEROSOL, SPRAY
Manufacturer: CVS Pharmacy
Category: otc | Type: HUMAN OTC DRUG LABEL
Date: 20260211

ACTIVE INGREDIENTS: MICONAZOLE NITRATE 1.3 g/130 g
INACTIVE INGREDIENTS: DISTEARDIMONIUM HECTORITE; ISOBUTANE; KAOLIN; ALCOHOL; ZEA MAYS SUBSP. MAYS WHOLE

CVS Jock Itch Spray

Active ingredient

Miconazole nitrate 2%

Purpose

Antifungal

Uses

- cures most jock itch (tinea cruris)
- relieves itching, buming and chafing associated with jock itch

Warnings

For external use only.

Flammable:

Do not use while smoking or near heat or flame. Do not puncture or incinerate. Contents under pressure, Do not store at temperature above 120'F. Intentional misuse by deliberately concentrating and inhaling contents can be harmful or fatal.

When using this product

- do not get into eyes or mouth
- use only as directed.

Stop use and ask a doctor if

- irritation occurs
- no improvement within 2 weeks

Do not use

on children under 2 years of age unless directed by a doctor.

Keep out of reach of children.

If swallowed, get medical help or contact a Poison Control Center right away.

Directions

- wash affected area and dry thoroughly
- shake can well and spray a thin layer over affected area twice daily (morning and night) or as directed by a doctor
- supervise children in the use of this product
- use daily for 2 weeks; If conditions persist, consult a doctor
- this product is not effective on the scalp or nails
- if nozzle clogs, clean with a pin

Other information

store between 20° and 30°C (68° and 86°F)

Inactive ingredient

Disteardimonium Hectorite, Isobutane, Kaolin, SD Alcohol 40-B, Zea Mays (Corn) Starch

Questions?

Call 1-866-964-0939

RECENT MAJOR CHANGES

.

Principal Display Panel

CVS

Health

Jock Itch

Spray

MICONAZOLE NITRATE 2%

Antifungal

Powder spray

- For the relief of itching,

chafing, scaling & burning

- Cures most jock itch
- Talc free

NET WT 4.6 OZ (130g)